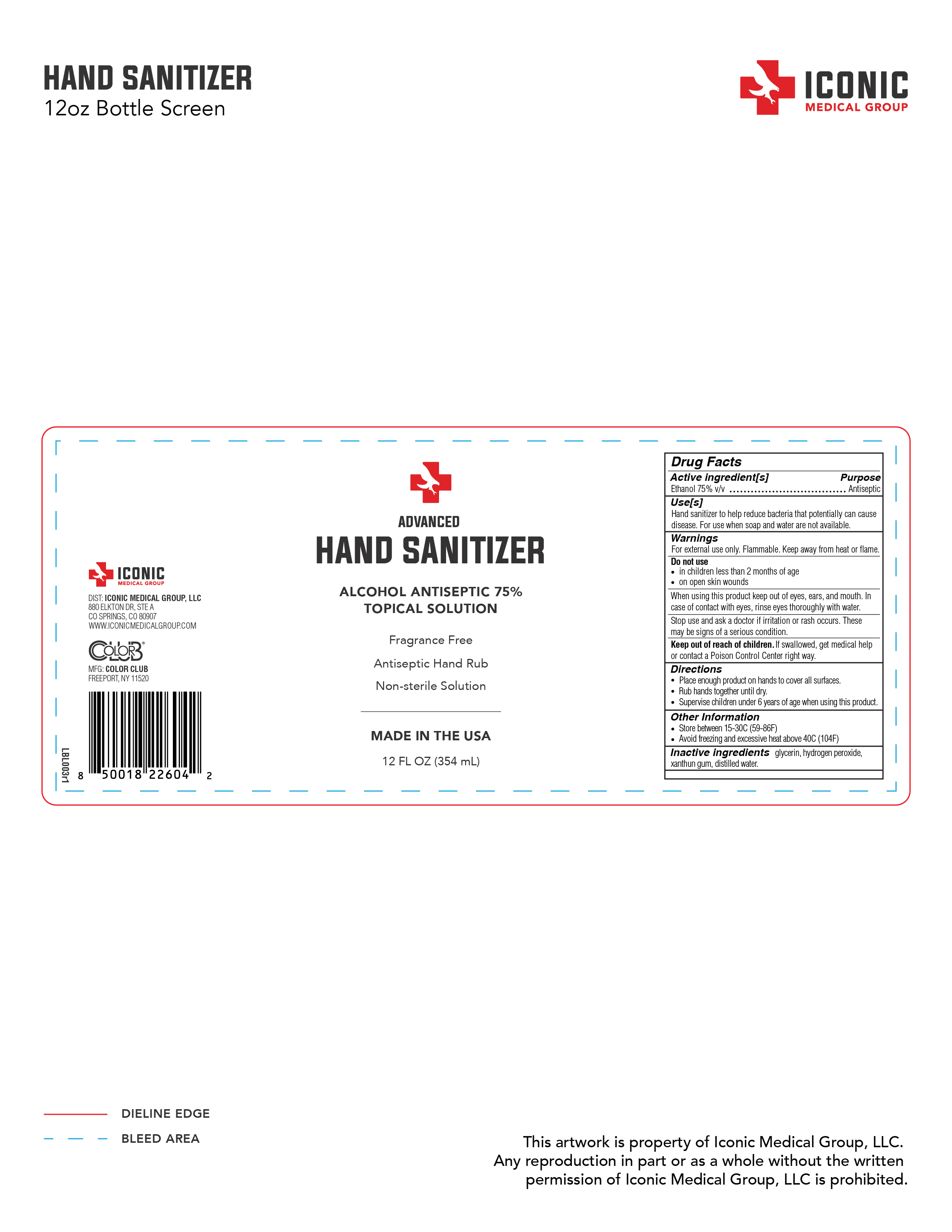 DRUG LABEL: Iconic Medical Group Hand Sanitizer - 12oz
NDC: 76909-0001 | Form: GEL
Manufacturer: Forsythe Cosmetic Group, Ltd.
Category: otc | Type: HUMAN OTC DRUG LABEL
Date: 20200428

ACTIVE INGREDIENTS: ALCOHOL 266.1615 mL/354.882 mL
INACTIVE INGREDIENTS: XANTHAN GUM 17.009712 mL/354.882 mL; HYDROGEN PEROXIDE 10.64646 mL/354.882 mL; GLYCERIN 10.64646 mL/354.882 mL

DOSAGE & ADMINISTRATION SECTION

354.882mL NDC: 76909-0001-1

- Place enough product on hands to cover all surfaces
- Rub hands until dry
- Supervise children under 6 years of age when using this product

WARNINGS SECTION

354.882mL NDC: 76909-0001-1

For external use only. Flammable. Keep away from heat or flame.

INACTIVE INGREDIENT SECTION

354.882mL NDC: 76909-0001-1

INACTIVE INGREDIENTS: glycerin, hydrogen peroxide, xanthum gum, distilled water

INDICATIONS & USAGE SECTION

354.882mL NDC: 76909-0001-1

Hand sanitizer to help reduce bacteria that potentially can cause disease. For use when soap and water are not available.

OTC - KEEP OUT OF REACH OF CHILDREN SECTION

354.882mL NDC: 76909-0001-1

Keep out of reach of children. If swallowed, get medical help or contact a Poison Control Center right away.

OTC - PURPOSE SECTION

354.882mL NDC: 76909-0001-1

Hand sanitzer to help reduce bacteria that can potentially cause disease. For use when soap and water are not available.

OTC - ACTIVE INGREDIENT SECTION

354.882mL NDC: 76909-0001-1

ACTIVE INGREDIENT(S)

Ethanol 75% v/v.................................Antiseptic

Full Bottle Label - 12oz

354.882mL NDC: 76909-0001-1